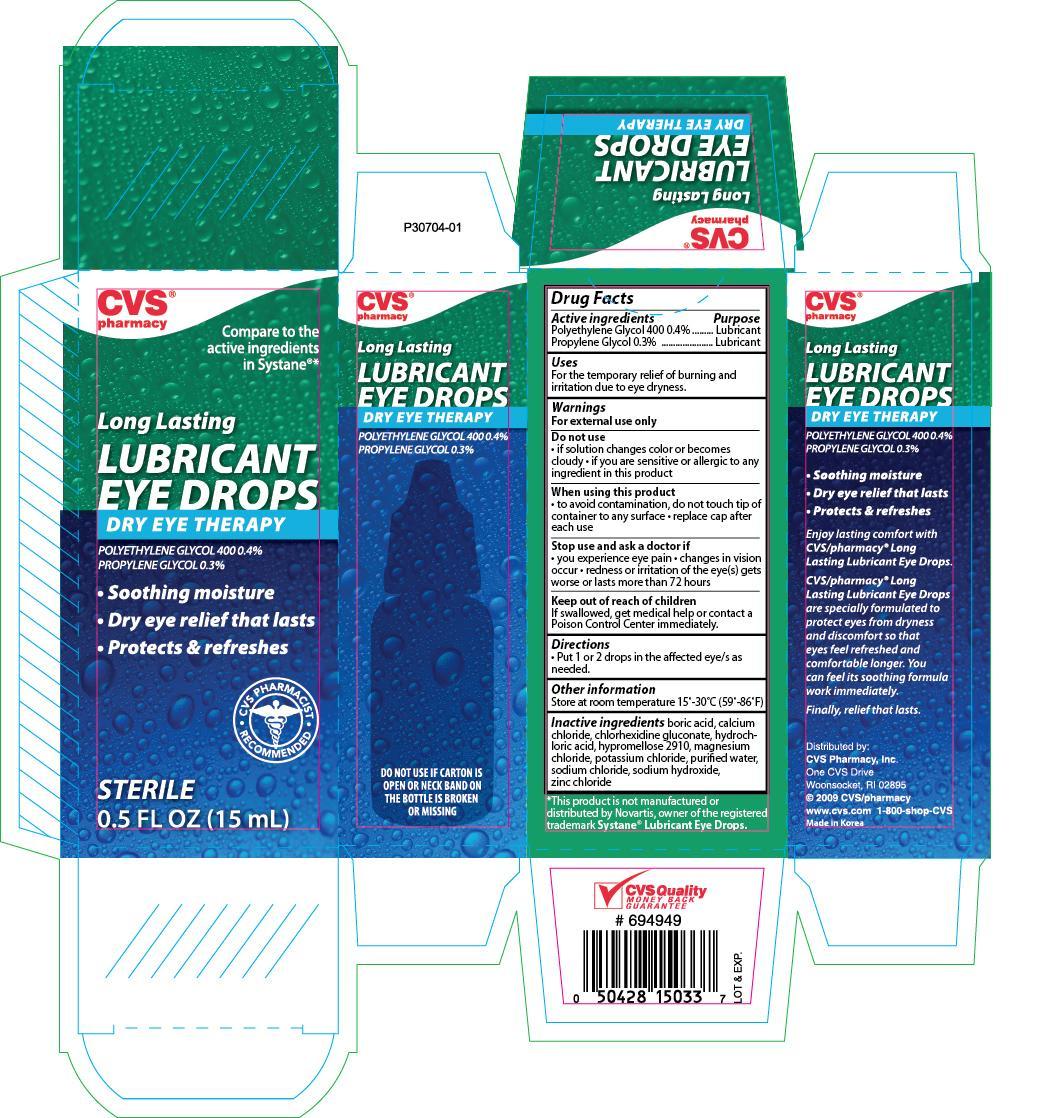 DRUG LABEL: CVS Long Lasting Lubricant Eye
NDC: 59779-151 | Form: SOLUTION/ DROPS
Manufacturer: CVS Pharmacy, Inc.
Category: otc | Type: HUMAN OTC DRUG LABEL
Date: 20171109

ACTIVE INGREDIENTS: POLYETHYLENE GLYCOL 400 0.4 mg/1 mg; PROPYLENE GLYCOL 0.3 mg/1 mg
INACTIVE INGREDIENTS: BORIC ACID; CALCIUM CHLORIDE; CHLORHEXIDINE GLUCONATE; HYDROCHLORIC ACID; MAGNESIUM CHLORIDE; POTASSIUM CHLORIDE; WATER; SODIUM CHLORIDE; SODIUM HYDROXIDE; ZINC CHLORIDE

CVS Lubricant Eye Drops 0.5oz (NBE Systane)

Drug Facts

Active ingredients Purpose

Polyethylene Glycol 400 0.4% Lubricant

Propylene Glycol 0.3% Lubricant

Uses

For the temporary relief of burning and irritation due to eye dryness.

Warnings

For external use only

Do not use

- if solution changes color or becomes cloudy
- if you are sensitive or allergic to any ingredient in this product

When using this product

- to avoid contamination, do not touch tip of container to any surface
- replace cap after each use

Stop use and ask a doctor if

- you experience eye pain
- changes in vision occur
- redness or irritation of the eye(s) gets worse or lasts more than 72 hours

Keep out of the reach of children

If swallowed, get medical help or contact a Poison Control Center immediately.

Directions

- Put 1 or 2 drops in the affected eye/s as needed.

Other information

- Store at room temperature 15°-30°C (59°-86°F)

INACTIVE INGREDIENT

Inactive ingredients boric acid, calcium chloride, chlorhexidine gluconate, hydrochloric acid, hypromellose 2910, magnesium chloride, potassium chloride, purified water, sodium chloride, sodium hydroxide, zinc chloride

DOSAGE AND ADMINISTRATION

Distributed By:

CVS Pharmacy, Inc.

One CVS Drive

Woonsocket, RI 02895

Made in Korea